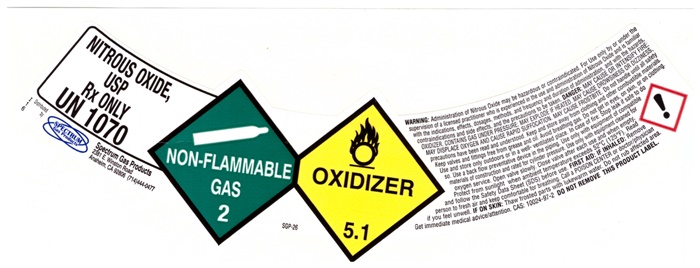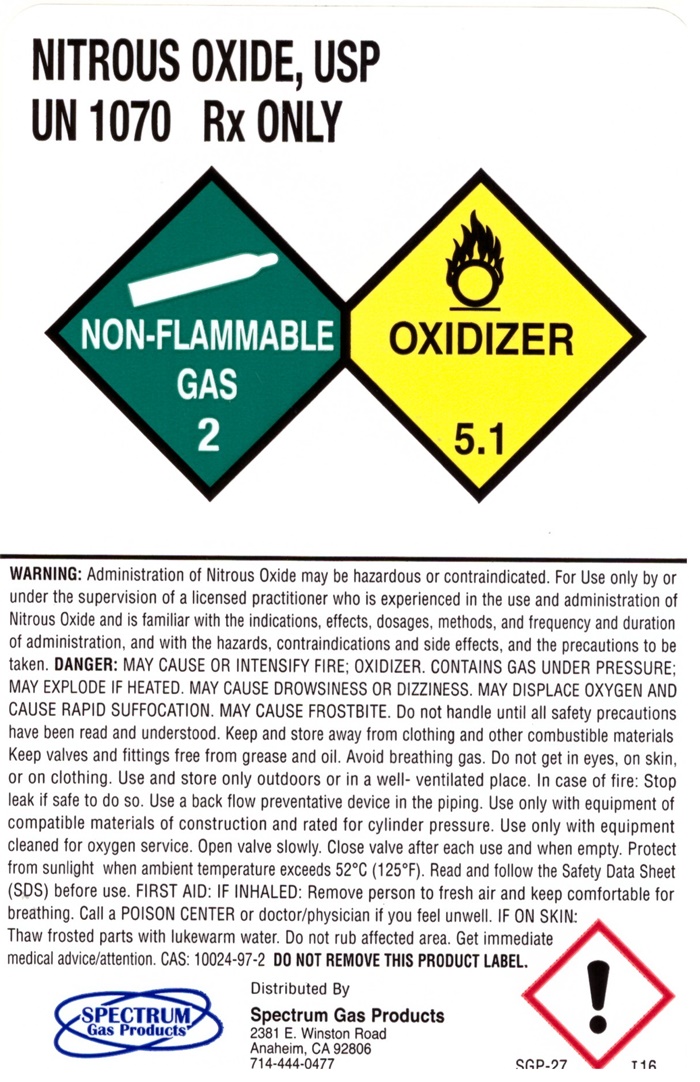 DRUG LABEL: NITROUS OXIDE
NDC: 67525-400 | Form: GAS
Manufacturer: Spectrum Gas Products, Inc
Category: prescription | Type: HUMAN PRESCRIPTION DRUG LABEL
Date: 20251203

ACTIVE INGREDIENTS: NITROUS OXIDE 99 L/100 L

Nitrous Oxide

Nitrous Oxide

USP

Rx ONLY

UN1070

NON-FLAMMABLE GAS 2 SGP-26 OXIDIZER 5.1

Spectrum Gas Products

2381 E. Winston Road

Anaheim, CA 92806

Rx only. WARNING: Administration of Nitrous Oxide may be hazardous or contraindicated. For use only by or under supervision of a licensed practitioner who is experienced in the use and administration of Nitrous Oxide and is familiar with the indications, effects, dosages, methods, and frequency and duration of administration, and with the hazards, contraindications, and side effects and the precautions to be taken. DANGER: MAY CAUSE OR INTENSIFY FIRE, OXIDIZER. CONTAINS GAS UNDER PRESSURE; MAY EXPLODE IF HEATED. MAY CAUSE DROWSINESS OR DIZZINESS. MAY DISPLACE OXYGEN AND CAUSE RAPID SUFFOCATION. MAY CAUSE FROSTBITE. Do not handle until all safety precautions have been rad and understood. Keep and store away from clothing and other combustible materials. Keep valves ad fittings free from grease and oil. Avoid breathing gas. Do not get in eyes, on skin, or on clothing. Use and store only outdoors or in a well-ventilated place. In case of fire: Stop leak if safe to do so. Use a back-flow preventive device in the piping. Use only with equipment of compatible materials of construction and rated for cylinder pressure. Use only with equipment cleaned for oxygen service. Open valve slowly. Close valve after each use and when empty. Protect from sunlight when ambient temperature exceeds 52oC (125oF). Read and follow the Safety Data Sheet (SDS) before use. FIRST AID: IF INHALED: Remove person to fresh air and keep comfortable for breathing. Call a POISON CENTER or doctor/physician if you feel unwell. IF ON SKIN: Thaw frosted parts with lukewarm water. Do not rub affected area. Get immediate medical advice/attention. CAS: 10024-97-2 DO NOT REMOVE THIS PRODUCT LABEL.